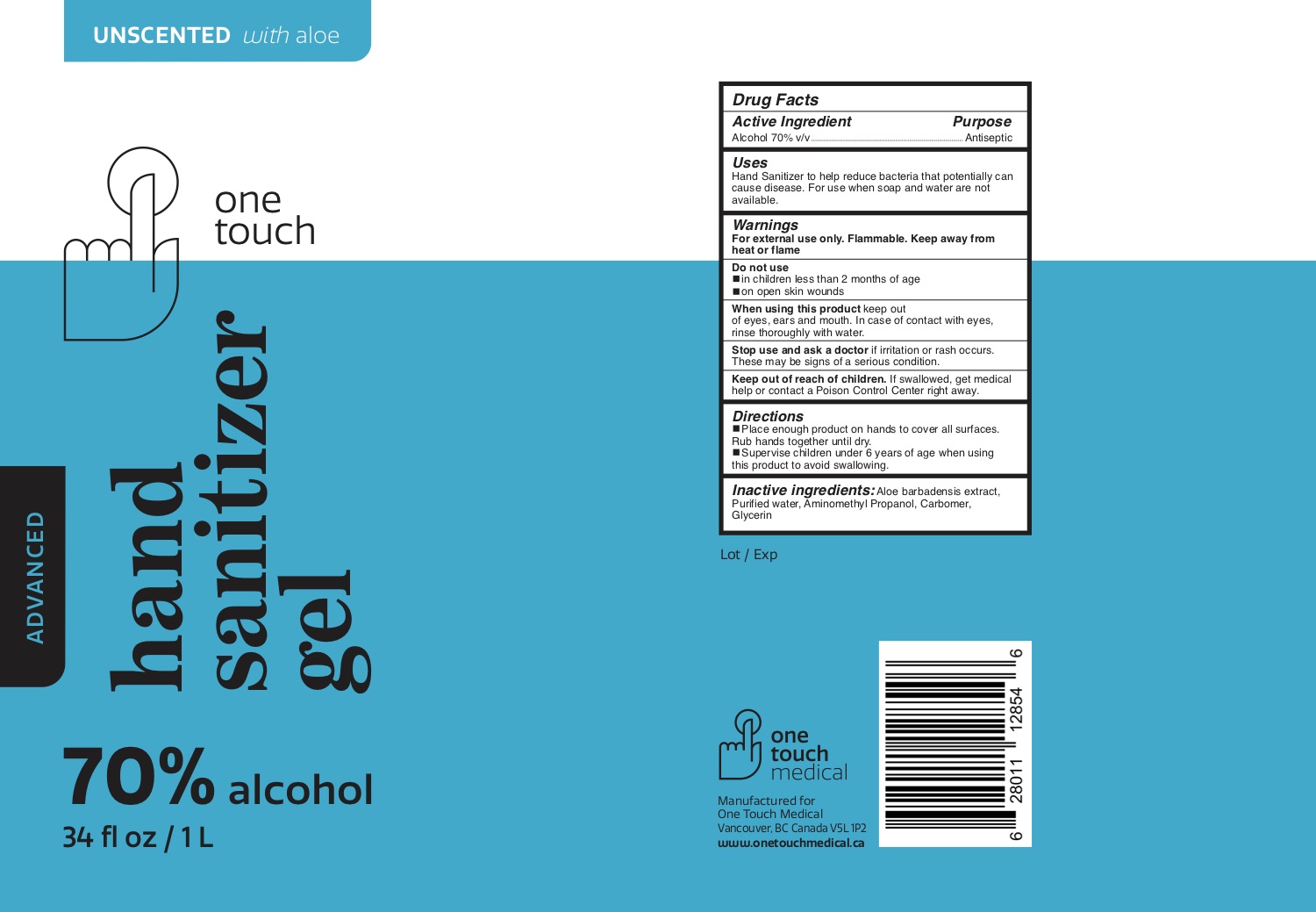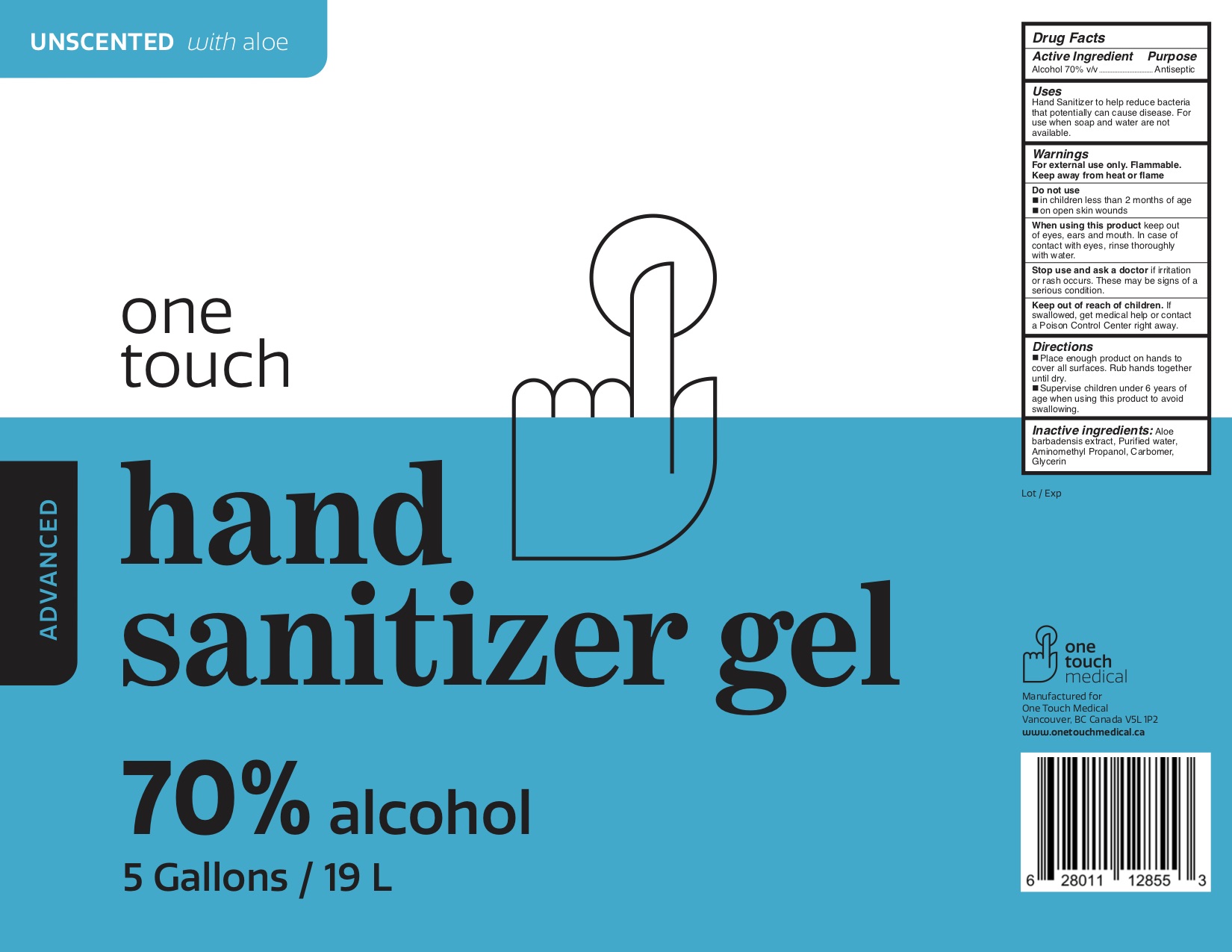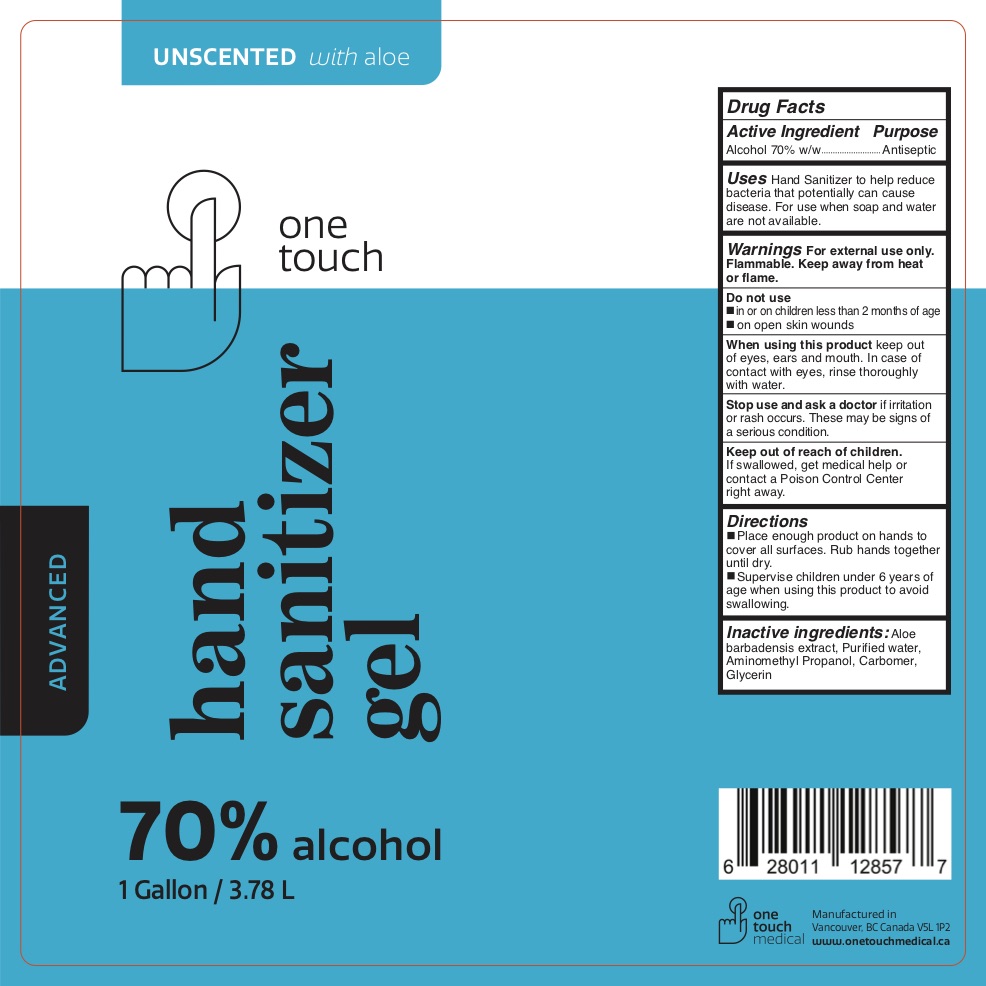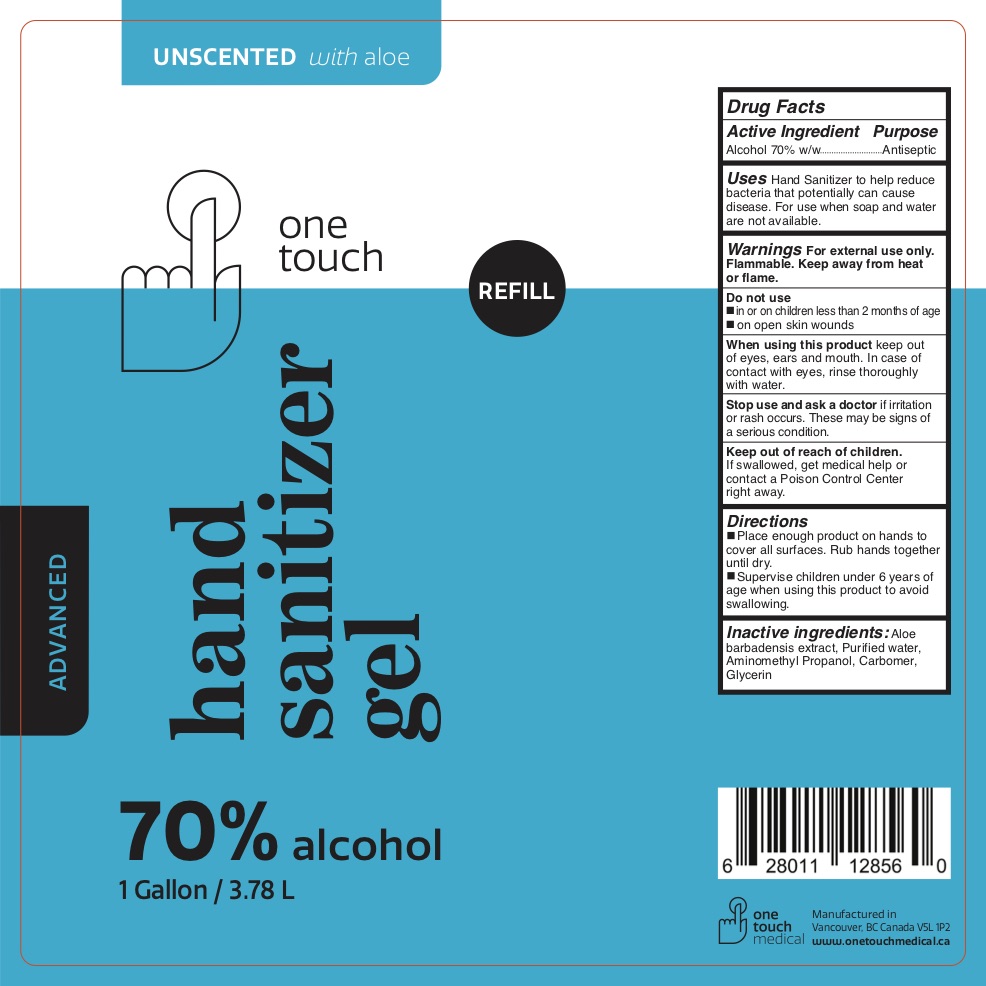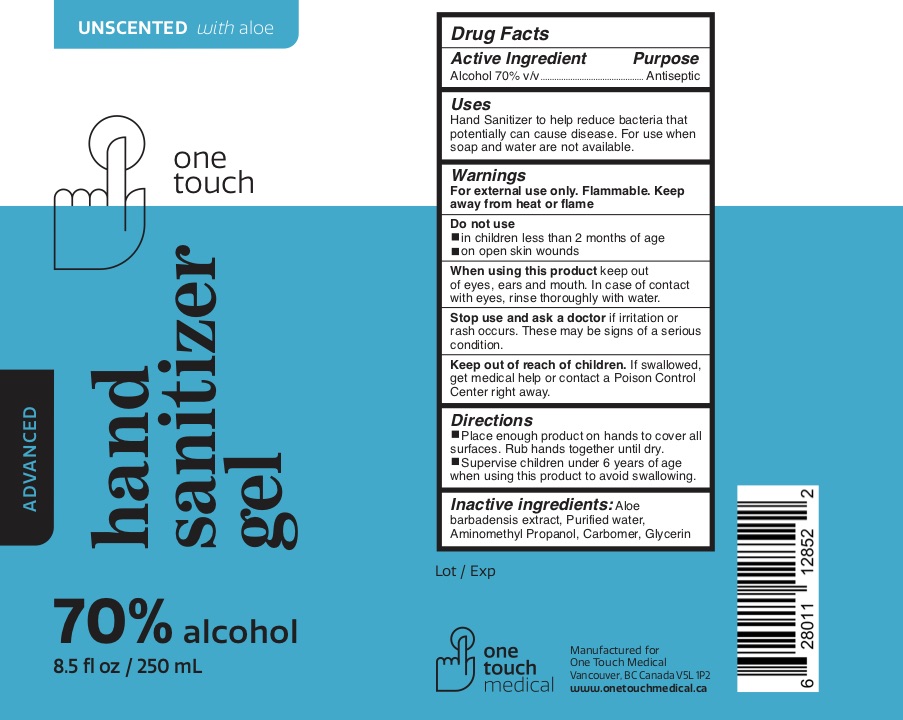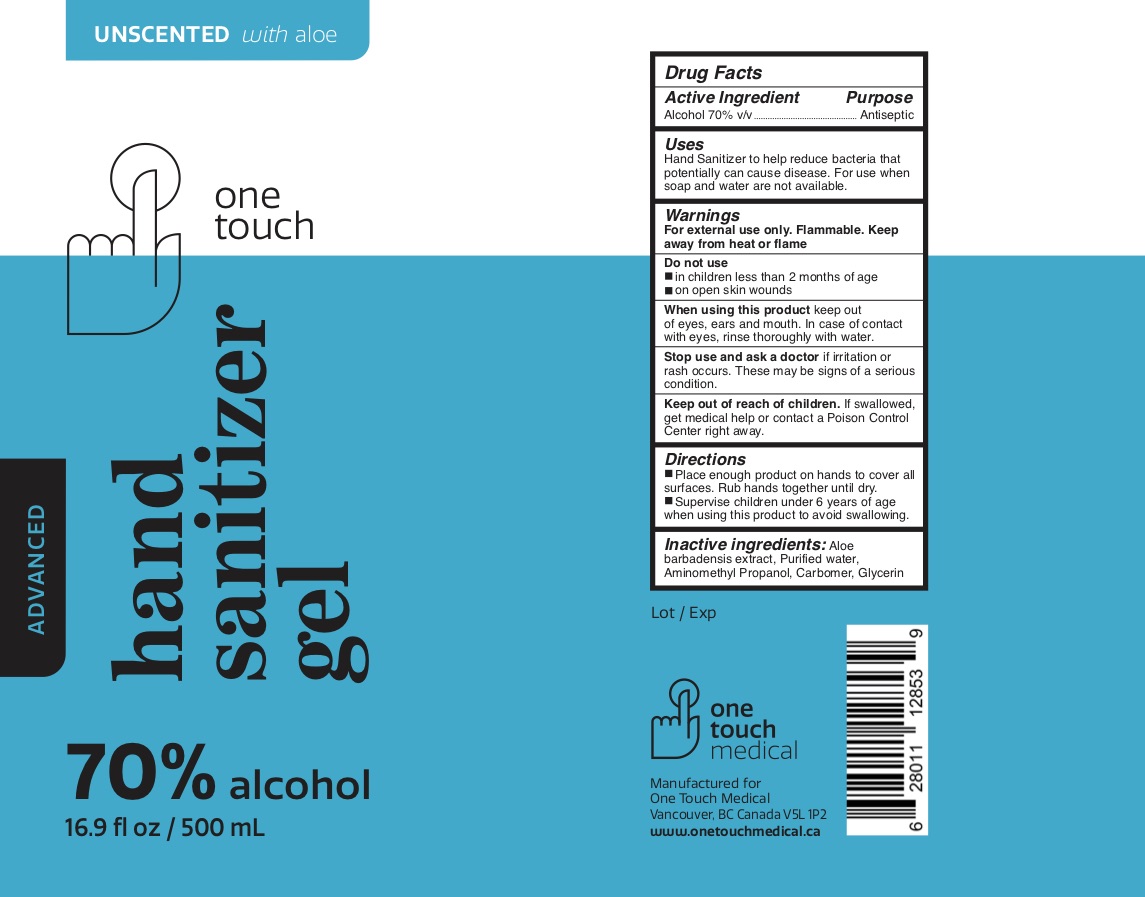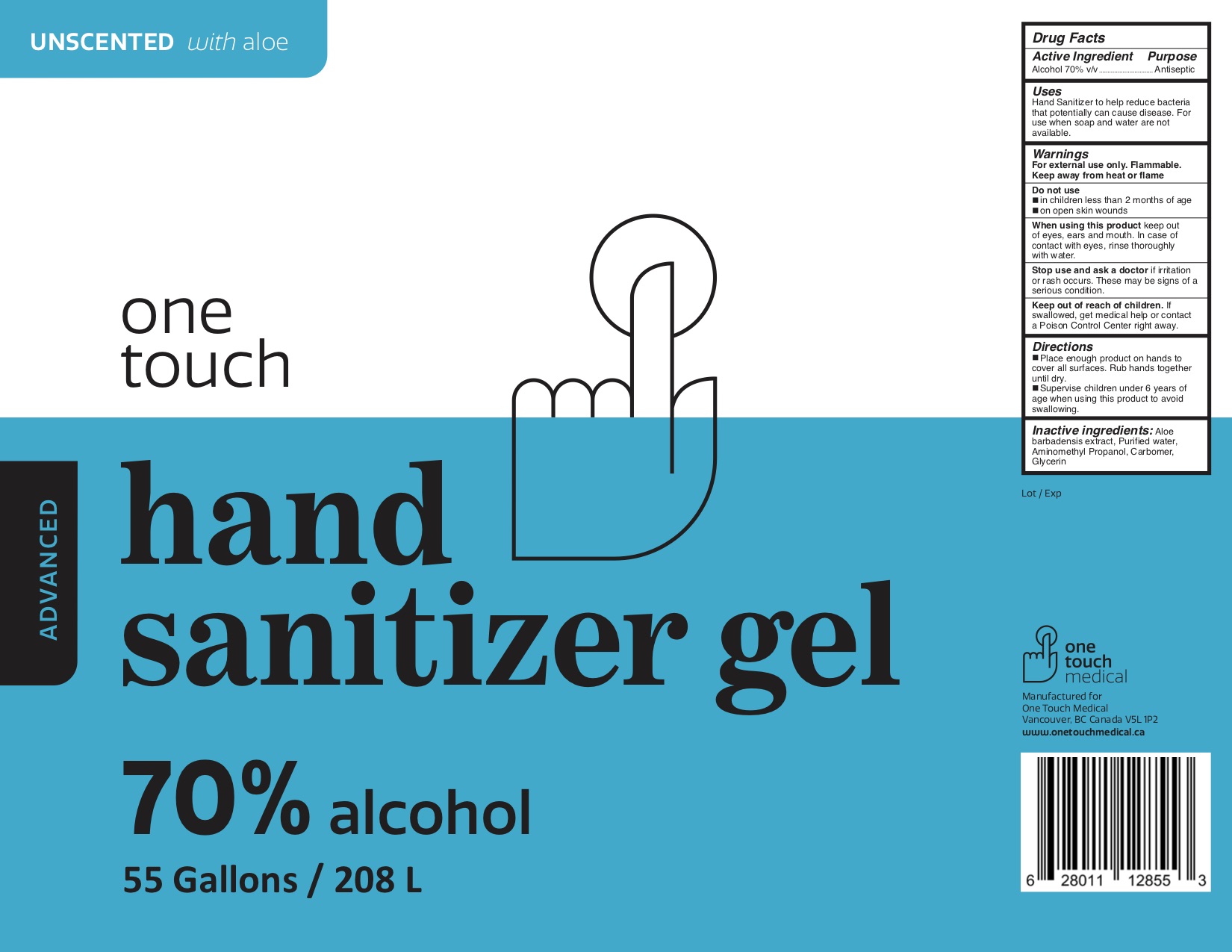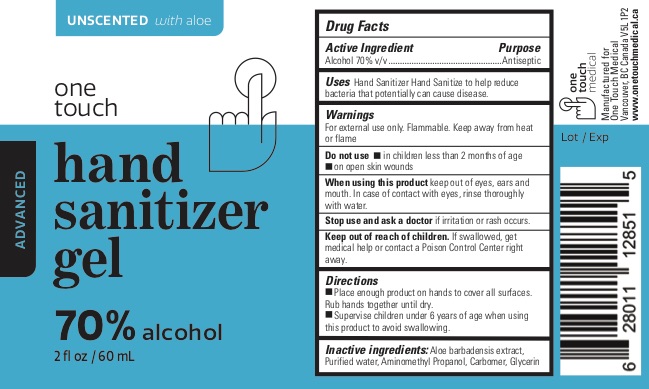 DRUG LABEL: One Touch Hand Sanitizer
NDC: 77301-604 | Form: GEL
Manufacturer: One Touch Medical Inc
Category: otc | Type: HUMAN OTC DRUG LABEL
Date: 20200717

ACTIVE INGREDIENTS: ALCOHOL 70 mL/100 mL
INACTIVE INGREDIENTS: GLYCERIN; WATER; ALOE; AMINOMETHYLPROPANOL; CARBOMER HOMOPOLYMER, UNSPECIFIED TYPE

One Touch Hand Sanitizer Gel

One Touch Hand Sanitizer Gel

Drug Facts

Purpose

Antiseptic

Use

Hand Sanitizer to help reduce bacteria that potentially can cause disease. For use when soap and water are not available.

Warnings

For external use only. Flammable. Keep away from heat or flame.

When using this product keep out of eyes, ears and mouth. In case of contact with eyes, rinse thoroughly with water.

Stop use and ask a doctor if irritation or rash occurs. These may be signs of a serious condition.

Keep out of reach of children. If swallowed, get medical help or contact a Poison Control Center right away.

Directions

- Place enough product on hands to cover all surfaces. Rub hands together until dry.
- Supervise children under 6 years of age when using this product to avoid swallowing.

Inactive ingredients

Aloe barbadensis extract, Purified water, Aminomethyl Propanol, Carbomer, Glycerin

Active ingredient

Alcohol 70% v/v

Do not use

- in children less than 2 months of age
- on open skin wounds

Package Label - Principal Display Panel

Made in Canada